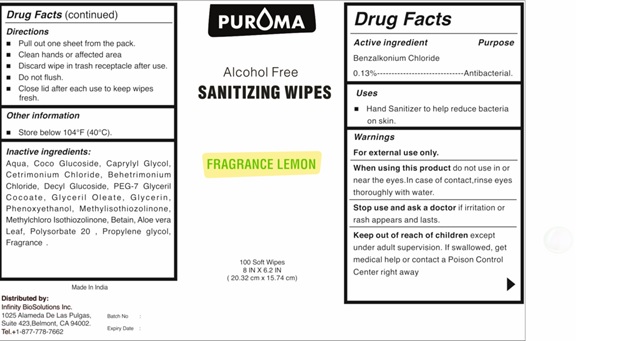 DRUG LABEL: PUROMA  Hand Sanitizer Wipe Alcohol Free with Fragrance
NDC: 80948-017 | Form: LIQUID
Manufacturer: ZENITH MICRO CONTROL
Category: otc | Type: HUMAN OTC DRUG LABEL
Date: 20240201

ACTIVE INGREDIENTS: BENZALKONIUM CHLORIDE 130 mg/100 mL
INACTIVE INGREDIENTS: WATER; METHYLCHLOROISOTHIAZOLINONE; GLYCERIN; METHYLISOTHIAZOLINONE; CETRIMONIUM CHLORIDE; PROPYLENE GLYCOL; CAPRYLYL GLYCOL; PHENOXYETHANOL; DECYL GLUCOSIDE; COCO GLUCOSIDE; GLYCERYL OLEATE; BEHENTRIMONIUM CHLORIDE; PEG-7 GLYCERYL COCOATE; POLYSORBATE 20; ALOE VERA LEAF; BETAINE; FRAGRANCE LEMON ORC2001060

Active ingredient

Benzalkonium chloride 0.13%

Purpose

Antibacterial

Uses

Hand Sanitizer to help reduce bacteria on skin.

Warnings

For external use only.
When using this productdo not use in or near the eyes. In case of contact, rinse eyes thoroughly with water.
Stop use and ask a doctor ifirritation or rash appears and lasts.

Keep out of reach of children

except under adult supervision. If swallowed, get medical help or contact a Poison Control Center right away.

Directions

• Pull out one sheet from the pack. Clean hands or affected area.
• Discard wipes in trash receptacle after use.
• Do not flush.
• Close lid after each used to keep wipes fresh.

Other information

Store below 104°F (40°C).

Inactive ingredients

Aqua, Coco Glucoside, Caprylyl Glycol, Cetrimonium Chloride, Behetrimonium Chloride, Decyl Glucoside, PEG-7 Glyceril Cocoate, Glyceril Oleate, Glycerin,Phenoxyethanol, Methylisothiozolinone, Methylchloro Isothiozolinone, Betain, Aloevera Leaf, Polysorbate 20 , Propylene glycol, Fragrance Lemon ORC2001060.